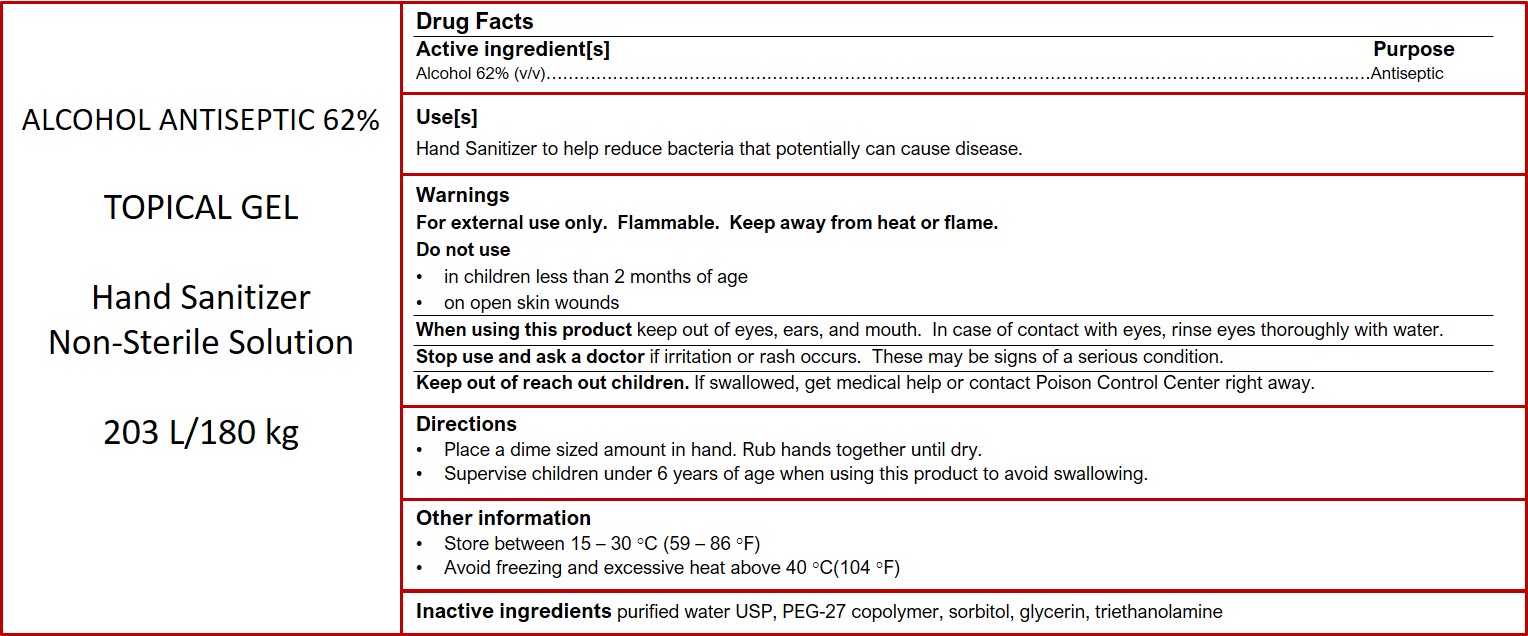 DRUG LABEL: Hand Sanitizing Gel
NDC: 75009-162 | Form: GEL
Manufacturer: Alpha Aromatics
Category: otc | Type: HUMAN OTC DRUG LABEL
Date: 20200430

ACTIVE INGREDIENTS: ALCOHOL 62 mL/100 mL
INACTIVE INGREDIENTS: TROLAMINE 0.7 mL/100 mL; GLYCERIN 0.6 mL/100 mL; WATER; ACRYLIC ACID/ISOPHORONE DIISOCYANATE/PEG-27 COPOLYMER 0.375 mL/100 mL; SORBITOL SOLUTION 0.6 mL/100 mL

Hand Sanitizing Gel 62% (v/v)

The hand sanitizer is manufactured in accordance with the recommendations in 21 CFR Part 333 for alcohol based topical antimicrobial OTC products for human use.

1. Alcohol(Ethanol) 62% (v/v).
2. Sorbitol 0.6% (v/v).
3. Gylcerin 0.6% (v/v).
4. PEG-27 copolymer 0.375% (v/v)
5. Triethanol 0.7% (v/v)
6. Sterile distilled water or boiled cold water.

The firm does not add other active or inactive ingredients. Different or additional ingredients may impact the quality and potency of the product.

Active Ingredient(s)

Alcohol 80% v/v. Purpose: Antiseptic

Purpose

Antiseptic, Hand Sanitizer

Use

Hand Sanitizer to help reduce bacteria that potentially can cause disease. For use when soap and water are not available.

Warnings

For external use only. Flammable. Keep away from heat or flame

Do not use

- in children less than 2 months of age
- on open skin wounds

When using this product keep out of eyes, ears, and mouth. In case of contact with eyes, rinse eyes thoroughly with water.
Stop use and ask a doctor if irritation or rash occurs. These may be signs of a serious condition.
Keep out of reach of children. If swallowed, get medical help or contact a Poison Control Center right away.

Stop use and ask a doctor if irritation or rash occurs. These may be signs of a serious condition.

Keep out of reach of children. If swallowed, get medical help or contact a Poison Control Center right away.

Directions

- Place enough product on hands to cover all surfaces. Rub hands together until dry.
- Supervise children under 6 years of age when using this product to avoid swallowing.

Other information

- Store between 15-30C (59-86F)
- Avoid freezing and excessive heat above 40C (104F)

Inactive ingredients

glycerin, hydrogen peroxide, purified water USP

Package Label - Principal Display Panel

203000 mL NDC: 75009-162-01

868300 mL NDC: 75009-162-02